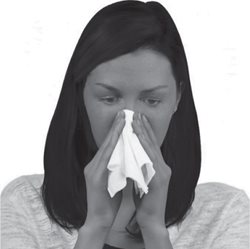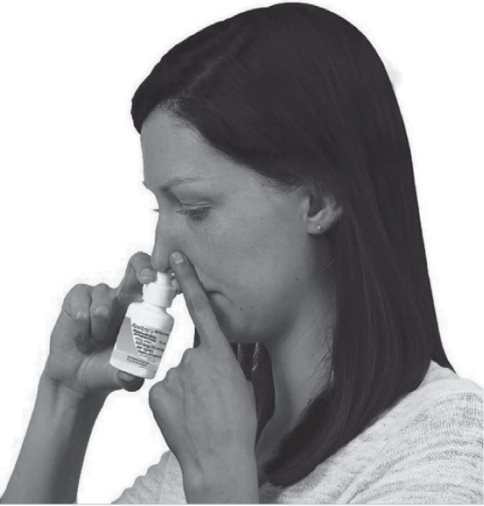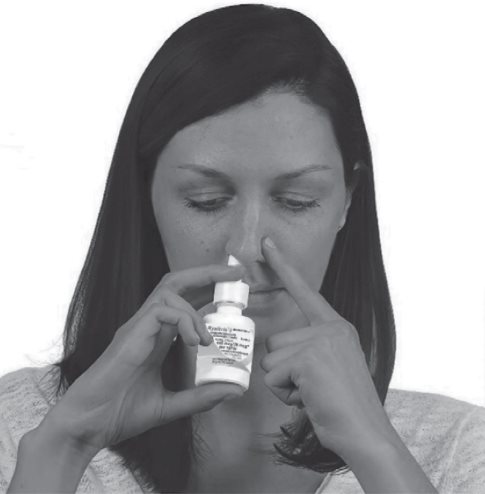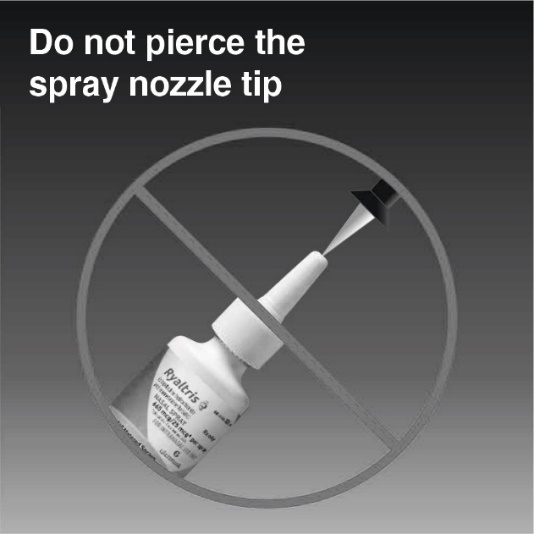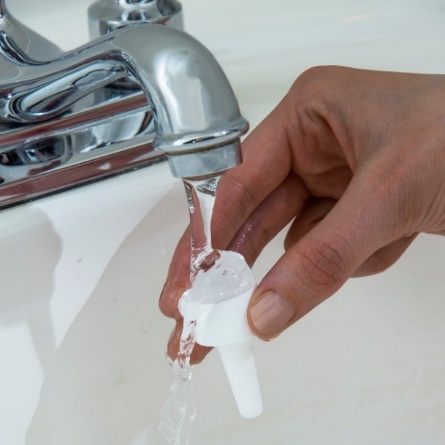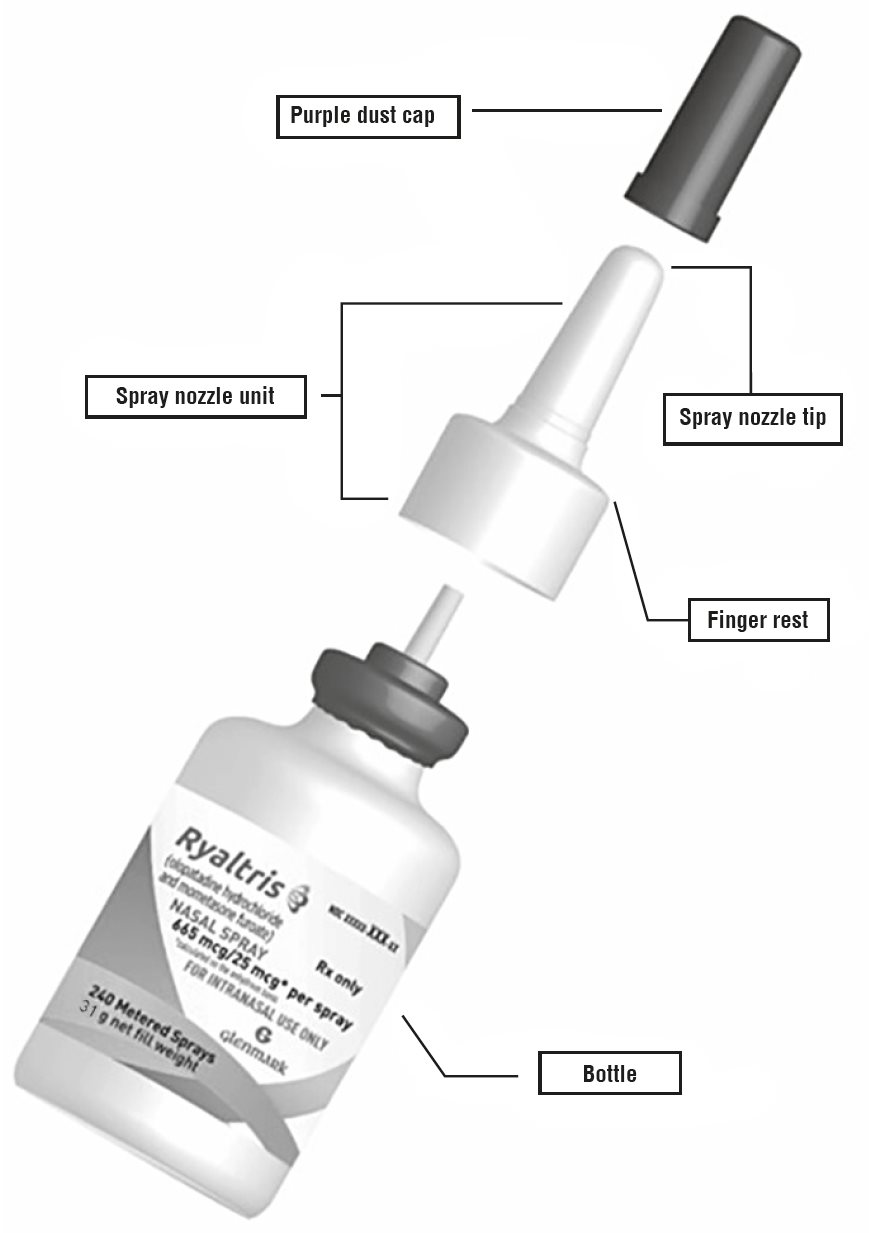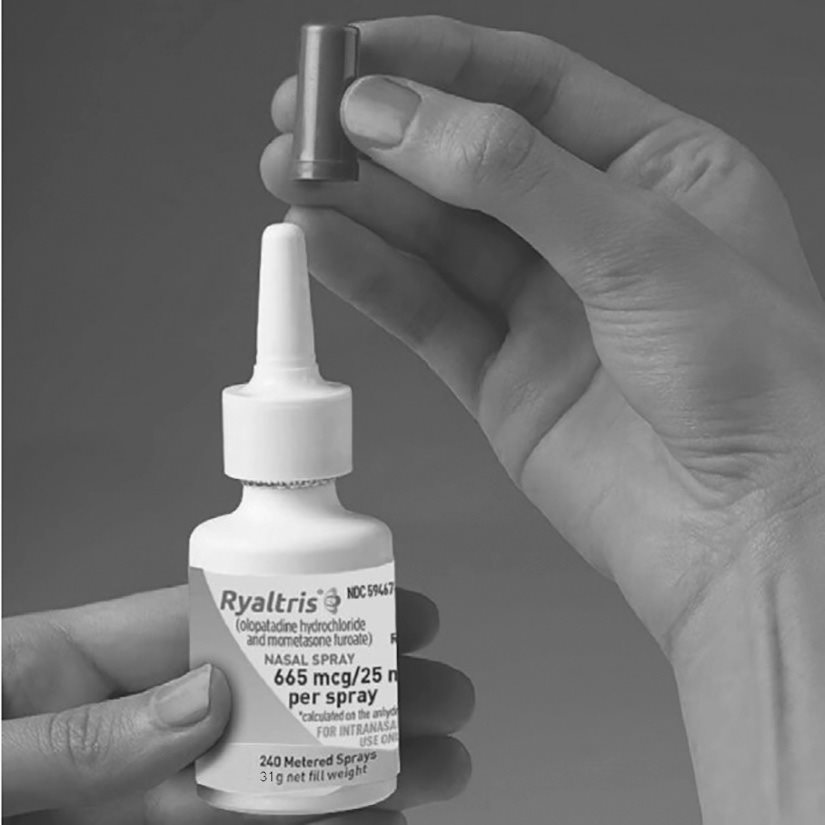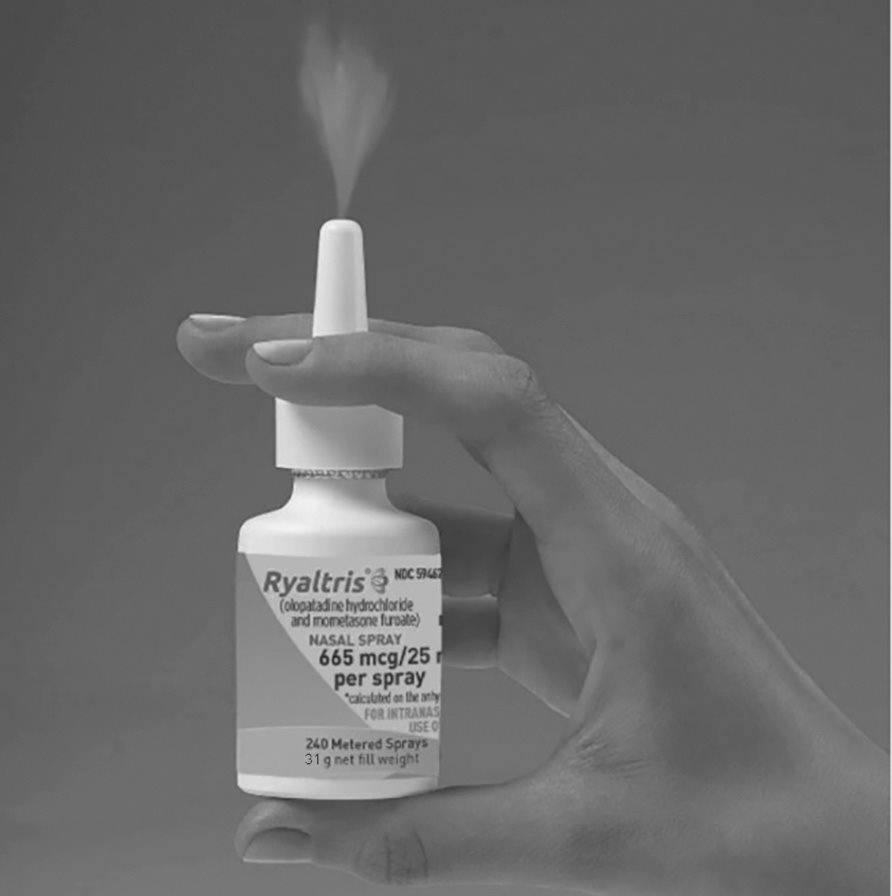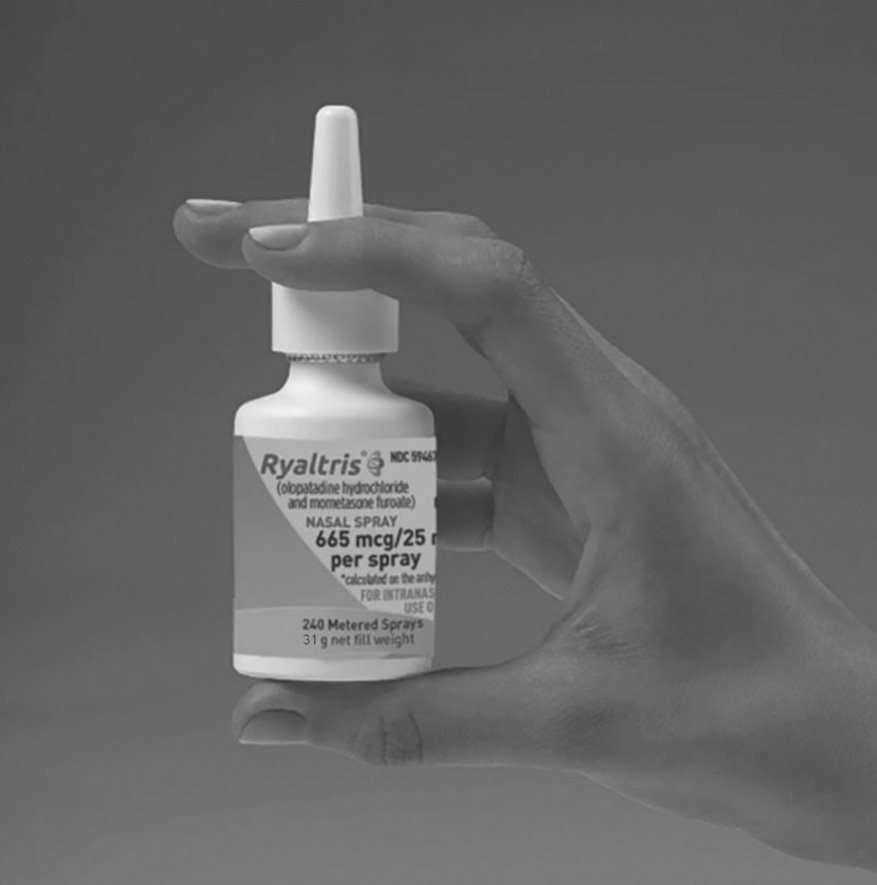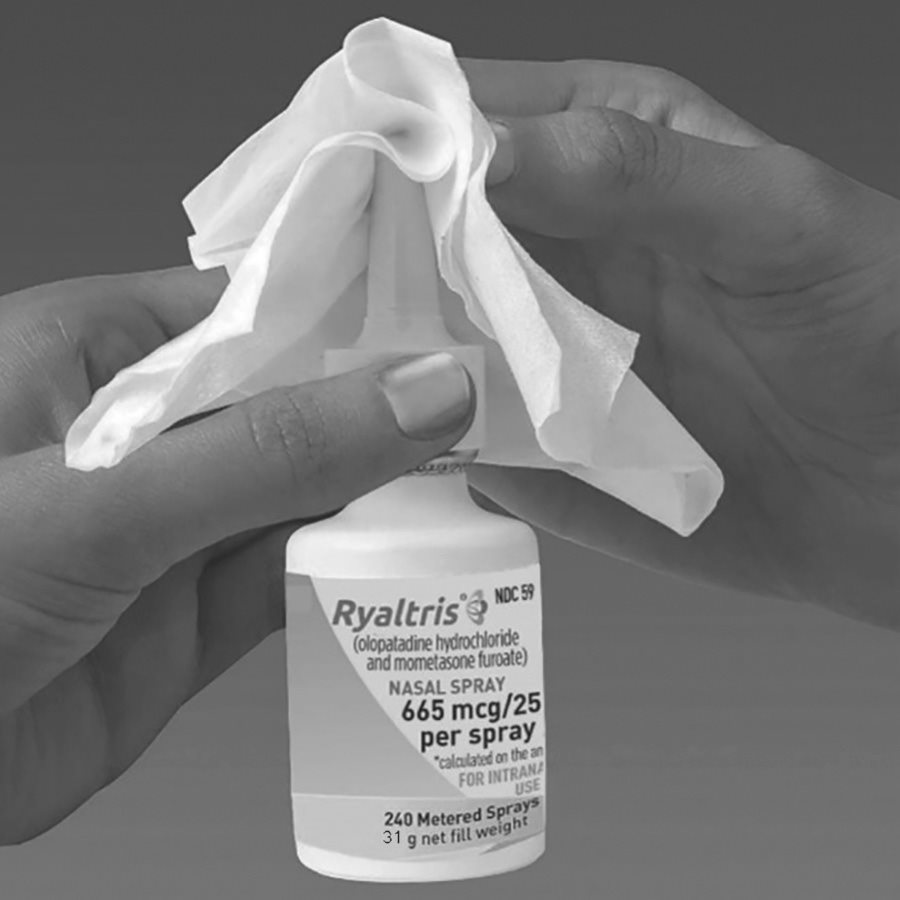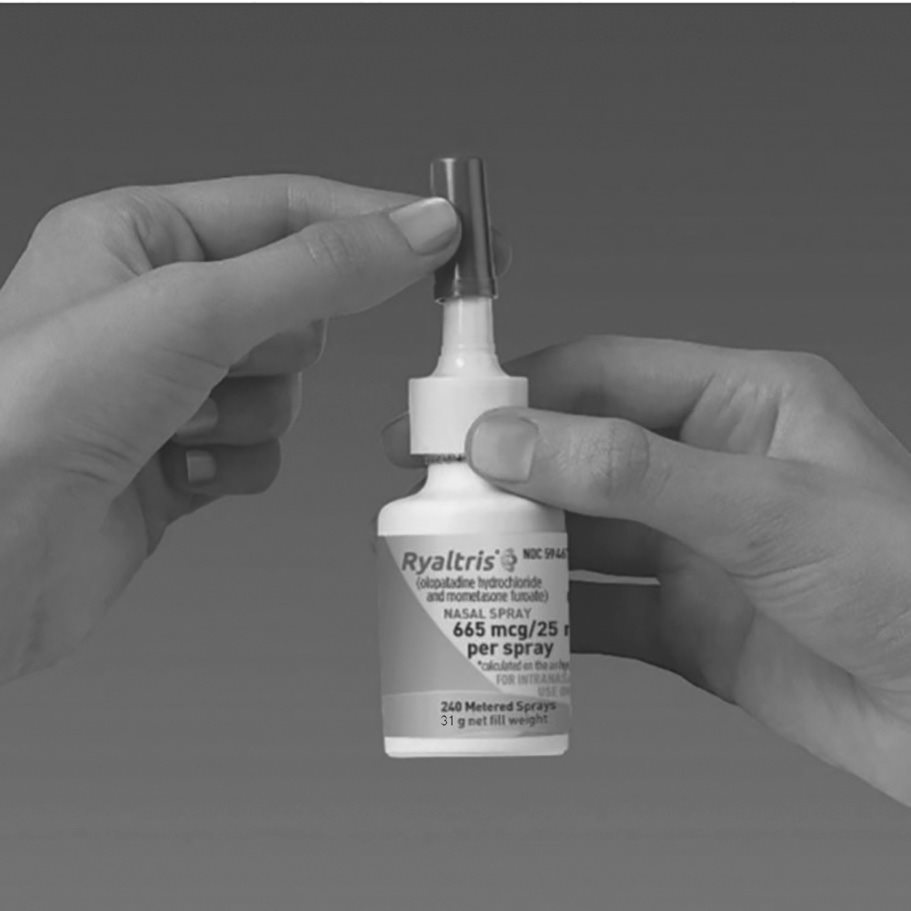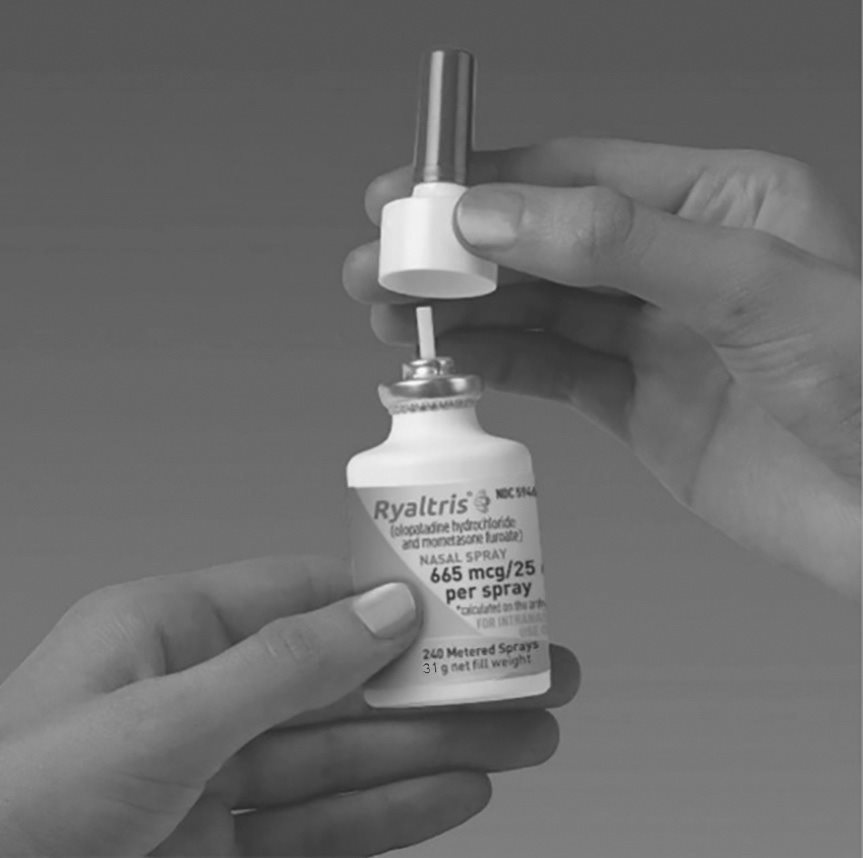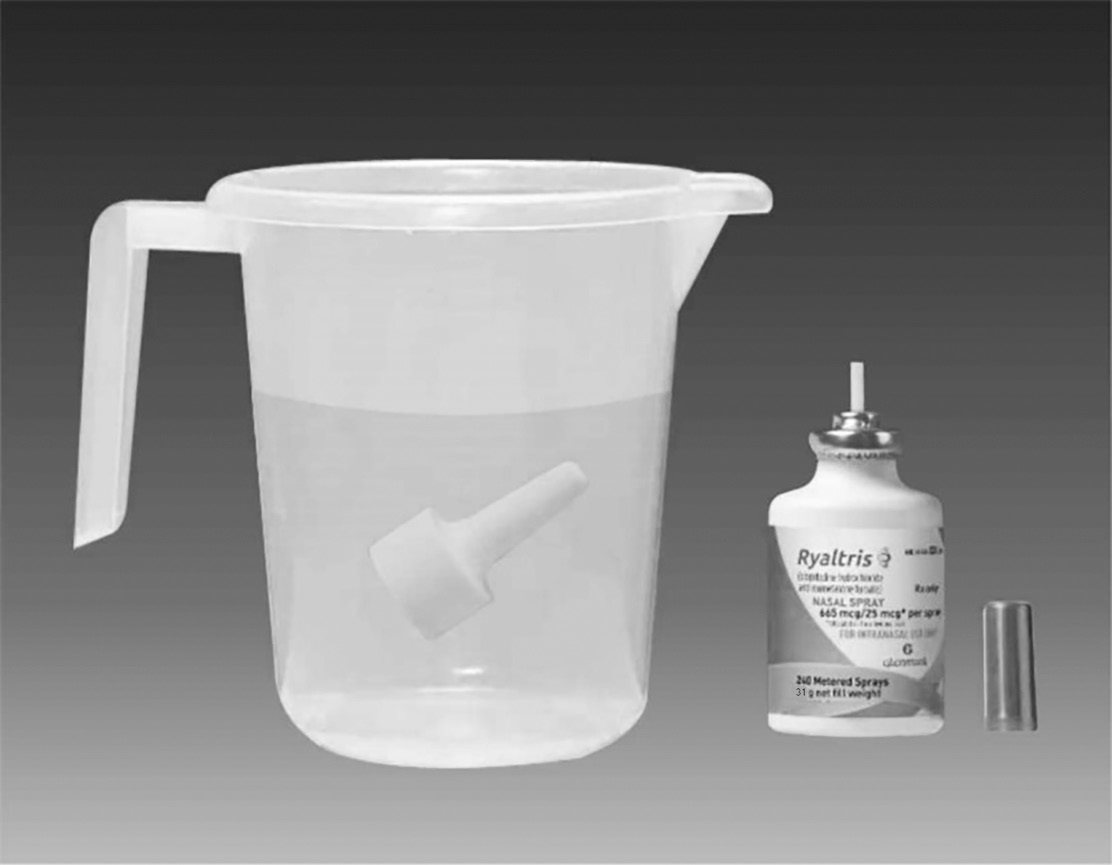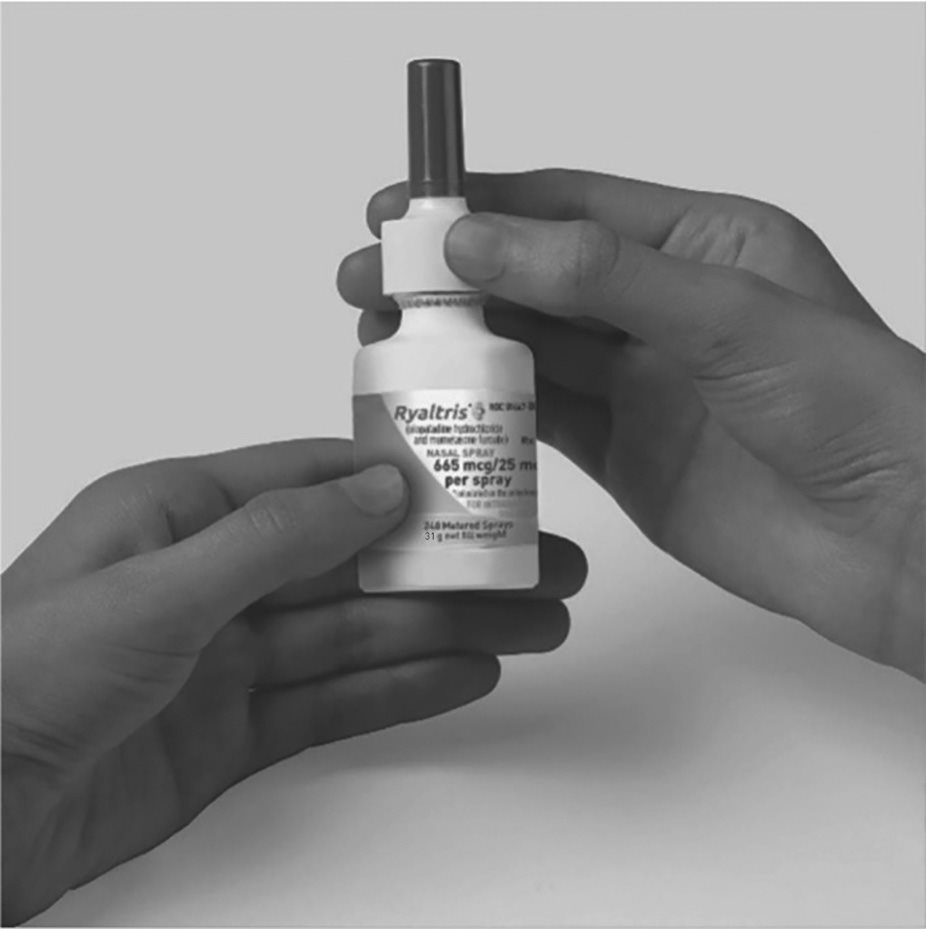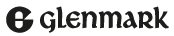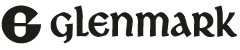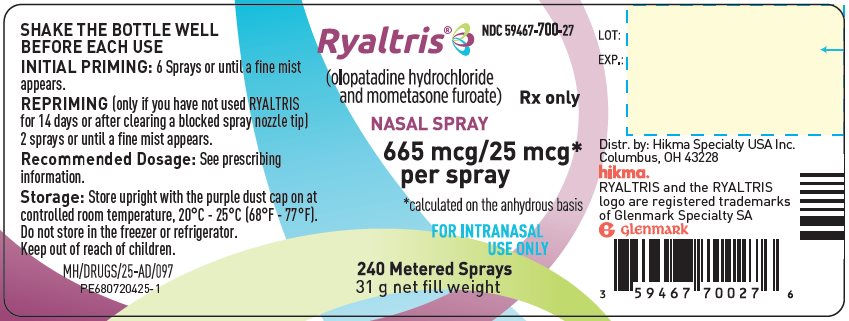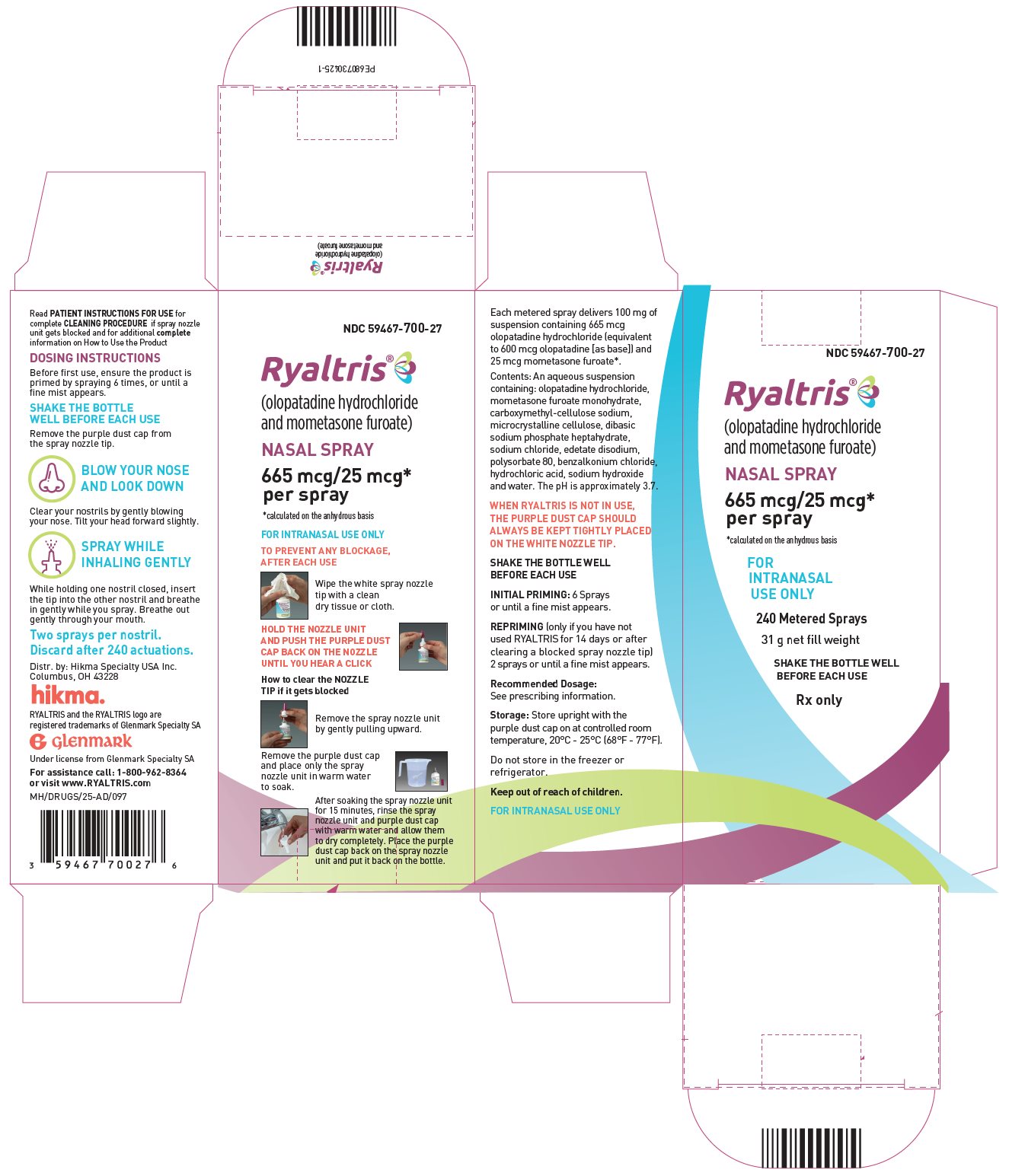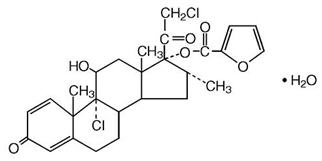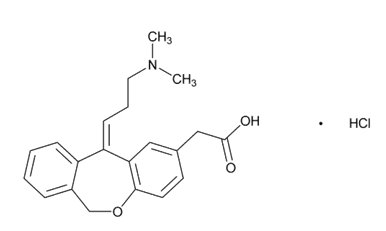 DRUG LABEL: Ryaltris
NDC: 59467-700 | Form: SPRAY, METERED
Manufacturer: HIKMA SPECIALTY USA INC.
Category: prescription | Type: HUMAN PRESCRIPTION DRUG LABEL
Date: 20260123

ACTIVE INGREDIENTS: OLOPATADINE HYDROCHLORIDE 665 ug/1 1; MOMETASONE FUROATE MONOHYDRATE 25 ug/1 1
INACTIVE INGREDIENTS: BENZALKONIUM CHLORIDE; CARBOXYMETHYLCELLULOSE SODIUM, UNSPECIFIED; SODIUM PHOSPHATE, DIBASIC, HEPTAHYDRATE; EDETATE DISODIUM; HYDROCHLORIC ACID; MICROCRYSTALLINE CELLULOSE; POLYSORBATE 80; SODIUM CHLORIDE; SODIUM HYDROXIDE; WATER

HIGHLIGHTS OF PRESCRIBING INFORMATION

These highlights do not include all the information needed to use RYALTRIS® safely and effectively. See full prescribing information for RYALTRIS.
RYALTRIS (olopatadine hydrochloride and mometasone furoate monohydrate nasal spray)
Initial U.S. Approval: 2022

1 INDICATIONS AND USAGE

RYALTRIS is a combination of olopatadine, a histamine-1 (H1)-receptor inhibitor, and mometasone furoate, a corticosteroid, indicated for the treatment of symptoms of seasonal allergic rhinitis in adult and pediatric patients 12 years of age and older. (1)

2 DOSAGE AND ADMINISTRATION

- For nasal use only (2)
- Recommended dosage: 2 sprays in each nostril twice daily (2)
- Prime before initial use by releasing 6 sprays or until a fine mist appears and when it has not been used for 14 or more days by releasing 2 sprays or until a fine mist appears. (2)

3 DOSAGE FORMS AND STRENGTHS

Nasal spray: 665 mcg of olopatadine hydrochloride and 25 mcg of mometasone furoate in each spray. (3)

4 CONTRAINDICATIONS

Patients with known hypersensitivity to any ingredients of RYALTRIS, including mometasone furoate. (4)

5 WARNINGS AND PRECAUTIONS

- Epistaxis, nasal ulcerations, nasal septal perforations, impaired wound healing, and Candida albicans infection: Monitor patients periodically for signs of adverse reactions on the nasal mucosa. (5.1)
- Somnolence: Avoid engaging in hazardous occupations requiring complete mental alertness and motor coordination such as driving or operating machinery when taking RYALTRIS. (5.2)
- Avoid concurrent use of alcohol or other central nervous system (CNS) depressants with RYALTRIS because additional reductions in alertness and additional impairment of CNS performance may occur. (5.2)
- Glaucoma and cataracts: Monitor patients with a change in vision or with a history of increased intraocular pressure, glaucoma, and/or cataracts. (5.3)
- Hypersensitivity Reactions: Hypersensitivity reactions can occur with RYALTRIS. Hypersensitivity reactions including wheezing, have occurred after the nasal administration of mometasone furoate. Discontinue RYALTRIS if such reactions occur. (5.4)
- Immunosuppression and Risk of Infections: Potential worsening of existing tuberculosis; fungal, bacterial, viral, or parasitic infections; or ocular herpes simplex. More serious or even fatal course of chickenpox or measles in susceptible patients: Use caution in patients with the above because of the potential for worsening of these infections. (5.5)
- Hypercorticism and adrenal suppression with misuse or use of higher-than-recommended dosages or at the regular dosage in susceptible patients at risk for such effects (5.6)
- Potential reduction in growth velocity in children: Routinely monitor the growth in pediatric patients receiving RYALTRIS. (5.7, 8.4)

6 ADVERSE REACTIONS

The most common adverse reactions (≥1% incidence) are dysgeusia, epistaxis, and nasal discomfort. (6.1)

To report SUSPECTED ADVERSE REACTIONS, contact Hikma Specialty USA Inc. at 1-800-962-8364 or FDA at 1-800-FDA-1088 or www.fda.gov/medwatch.

FULL PRESCRIBING INFORMATION

1 INDICATIONS AND USAGE

RYALTRIS is indicated for the treatment of symptoms of seasonal allergic rhinitis in adult and pediatric patients 12 years of age and older.

2 DOSAGE AND ADMINISTRATION

For nasal use only.

The recommended dosage of RYALTRIS is 2 sprays (2 sprays deliver a total of 1,330 mcg of olopatadine hydrochloride and 50 mcg of mometasone furoate) in each nostril twice daily.

- Shake the bottle well before each use.
- Prime RYALTRIS before initial use by releasing 6 sprays or until a fine mist appears. When RYALTRIS has not been used for 14 or more days, re-prime by releasing 2 sprays or until a fine mist appears.
- Avoid spraying RYALTRIS into the eyes or mouth.

3 DOSAGE FORMS AND STRENGTHS

Nasal spray: 665 mcg of olopatadine hydrochloride and 25 mcg of mometasone furoate in each spray

4 CONTRAINDICATIONS

RYALTRIS is contraindicated in patients with known hypersensitivity to any ingredients of RYALTRIS. Hypersensitivity reactions, including wheezing, has occurred after nasal administration of mometasone furoate [see Warnings and Precautions (5.4)].

5 WARNINGS AND PRECAUTIONS

5.1 Local Nasal Adverse Reactions

Epistaxis

Epistaxis was observed in 1% of patients treated with RYALTRIS and 0.6% of patients who received placebo in 2-week studies in patients with seasonal allergic rhinitis [see Adverse Reactions (6.1)].

Nasal Ulceration and Nasal Septal Perforation

Instances of nasal ulceration and nasal septal perforation have occurred in patients following the nasal application of antihistamines such as RYALTRIS.

Monitor patients periodically for signs of adverse effects on the nasal mucosa.

Impaired Nasal Wound Healing

Because of the inhibitory effect of corticosteroids on wound healing, patients who have experienced recent nasal septal ulcers, nasal surgery, or nasal trauma should avoid use of RYALTRIS until healing has occurred.

Local Candida Infection

Localized infections of the nose and pharynx with Candida albicans have occurred from nasal administration of mometasone furoate.

When such an infection occurs, discontinue RYALTRIS and institute appropriate local or systemic therapy. Patients using RYALTRIS over several months or longer should be examined periodically for evidence of Candida infection.

5.2 Somnolence and Impaired Mental Alertness

Patients should be cautioned against engaging in hazardous occupations requiring complete mental alertness and motor coordination, such as operating machinery or driving a motor vehicle, after administration of RYALTRIS. Concurrent use of RYALTRIS with alcohol or other central nervous system (CNS) depressants should be avoided because additional reductions in alertness and additional impairment of CNS performance may occur.

Somnolence was reported in 0.3% of patients treated with RYALTRIS and none of the patients who received placebo in 2-week studies in patients with seasonal allergic rhinitis [see Adverse Reactions (6.1)].

5.3 Glaucoma and Cataracts

Nasal and inhaled corticosteroids including RYALTRIS can result in the development of glaucoma and/or cataracts. Therefore, close monitoring is warranted in patients with a change in vision or with a history of increased intraocular pressure, glaucoma, and/or cataracts.

5.4 Hypersensitivity Reactions

Hypersensitivity reactions can occur with RYALTRIS. Hypersensitivity reactions including wheezing, have occurred after the nasal administration of mometasone furoate. Discontinue RYALTRIS if such reactions occur [see Contraindications (4)].

5.5 Immunosuppression and Risk of Infections

Persons who are using drugs that suppress the immune system, such as corticosteroids, including RYALTRIS, are more susceptible to infections than healthy individuals. Chickenpox and measles, for example, can have a more serious or even fatal course in susceptible children or adults using corticosteroids. In children or adults who have not had these diseases or been properly immunized, particular care should be taken to avoid exposure. How the dose, route, and duration of corticosteroid administration affect the risk of developing a disseminated infection is not known. The safety and effectiveness of RYALTRIS have not been established in pediatric patients less than 12 years of age and RYALTRIS is not indicated for use in this population. The contribution of the underlying disease and/or prior corticosteroid treatment to the risk is also not known. If exposed to chickenpox, prophylaxis with varicella zoster immune globulin (VZIG) may be indicated. If exposed to measles, prophylaxis with pooled intramuscular immunoglobulin (IG) may be indicated (see the respective Prescribing Information for VZIG and IG). If chickenpox develops, treatment with antiviral agents may be considered.

Corticosteroids should be used with caution, if at all, in patients with active or quiescent tuberculous infections of the respiratory tract, untreated local or systemic fungal or bacterial infections, systemic viral or parasitic infections, or ocular herpes simplex because of the potential for worsening of these infections.

5.6 Hypercorticism and Adrenal Suppression

Hypercorticism and adrenal suppression may occur when nasal corticosteroids, including RYALTRIS, are misused by taking higher-than-recommended dosages [see Dosage and Administration (2)] or in patients at risk for such effects.

5.7 Effect on Growth

Nasal corticosteroids, including RYALTRIS, may cause a reduction in growth velocity when administered to pediatric patients. The safety and effectiveness of RYALTRIS have not been established in pediatric patients less than 12 years of age and RYALTRIS is not indicated for use in this population. Routinely monitor the growth of pediatric patients receiving RYALTRIS [see Use in Specific Populations (8.4)].

6 ADVERSE REACTIONS

The following clinically significant adverse reactions are described elsewhere in labeling:

- Local Nasal Adverse Reactions [see Warnings and Precautions (5.1)]
- Somnolence and Impaired Mental Alertness [see Warnings and Precautions (5.2)]
- Glaucoma and Cataracts [see Warnings and Precautions (5.3)]
- Hypersensitivity Reactions [see Warnings and Precautions (5.4)]
- Immunosuppression and Risk of Infections [see Warnings and Precautions (5.5)]
- Hypercorticism and Adrenal Suppression [see Warnings and Precautions (5.6), Use in Specific Populations (8.4)]
- Effect on Growth [see Warnings and Precautions (5.7)]

6.1 Clinical Trials Experience

Because clinical studies are conducted under widely varying conditions, adverse reaction rates observed in the clinical studies of a drug cannot be directly compared with rates in the clinical studies of another drug and may not reflect the rates observed in practice.

Adults and Pediatric Patients 12 Years of Age and Older

The pooled RYALTRIS safety population reflects exposure to RYALTRIS at 2 sprays (2 sprays deliver a total of 1,330 mcg of olopatadine hydrochloride and 50 mcg of mometasone furoate) in each nostril twice daily in a total of 1189 patients from Studies 1 and 2 [see Clinical Studies (14)] and from three additional placebo and/or active-controlled studies in patients with allergic rhinitis. One placebo controlled study was a 52-week safety study. In this study, 393 patients were exposed to RYALTRIS for one year, and no new safety signals were observed.

The RYALTRIS safety population described below reflects exposure to RYALTRIS at 2 sprays (2 sprays deliver a total of 1,330 mcg of olopatadine hydrochloride and 50 mcg of mometasone furoate) in each nostril twice daily for two weeks duration in a total of 789 patients, including 596 patients from Studies 1 and 2 [see Clinical Studies (14)], and 36 and 157 from two additional placebo and active-controlled studies in patients with seasonal allergic rhinitis. The demographics of the RYALTRIS-treated patients were 12 to 81 years of age (mean age of 40 years; 67% female; 81% White, 15% Black/African American and 3% Other).

Table 1 lists adverse reactions from the safety population reported with frequencies ≥1% and more frequently than placebo in patients treated with RYALTRIS. Somnolence was reported in <1% (2 of 789) of patients treated with RYALTRIS and no patients treated with placebo.

Table 1: Adverse Reactions with ≥1% Incidence that Were Reported More Frequently with RYALTRIS than Placebo in the Safety Population in Adult and Pediatric Patients 12 Years of Age and Older with Seasonal Allergic Rhinitis
 | RYALTRIS N=789 n (%) | Olopatadine HCl Nasal Spray* N=751 n (%) | Mometasone Furoate Nasal Spray* N=746 n (%) | Placebo N=776 n (%)
Dysgeusia | 24 (3.0) | 16 (2.1) | 0 (0) | 2 (0.3)
Epistaxis | 8 (1.0) | 11 (1.5) | 6 (0.8) | 5 (0.6)
Nasal discomfort | 8 (1.0) | 4 (0.5) | 4 (0.5) | 6 (0.8)

* Non-US approved drugs

7 DRUG INTERACTIONS

No formal drug-drug interaction studies have been performed with RYALTRIS. The drug interactions of the combination are expected to reflect those of the individual components [see Clinical Pharmacology (12.3)].

7.1 Central Nervous System Depressants

Concurrent use of RYALTRIS with alcohol or other central nervous system depressants should be avoided because somnolence and impairment of central nervous system performance may occur [see Warnings and Precautions (5.2)].

7.2 Inhibitors of Cytochrome P450 3A4

Studies have shown that mometasone furoate, a component of RYALTRIS, is primarily and extensively metabolized to multiple metabolites. In vitro studies have confirmed the primary role of cytochrome P450 (CYP) 3A4 in the metabolism of this compound.

Concomitant administration of CYP3A4 inhibitors may inhibit the metabolism of, and increase the mometasone furoate plasma concentration and potentially increase the risk for adverse reactions. Caution should be exercised when considering the coadministration of RYALTRIS with strong CYP3A4 inhibitors [see Clinical Pharmacology (12.3)].

8 USE IN SPECIFIC POPULATIONS

8.1 Pregnancy

Risk Summary

There are no available data on RYALTRIS or mometasone furoate use in pregnant women to evaluate for a drug-associated risk of major birth defects, miscarriage or other adverse maternal or fetal outcomes.

Postmarketing experience with antihistamines, with similar mechanism of action to olopatadine, have not identified a drug-associated risk of major birth defects, miscarriage, or adverse maternal or fetal outcomes. However, there are no published human data specific to olopatadine.

Animal reproduction studies have not been conducted with RYALTRIS. However, animal reproduction studies are available for olopatadine hydrochloride and mometasone furoate. Oral administration of olopatadine hydrochloride to pregnant rats and rabbits caused a decrease in the number of live fetuses at maternal doses approximately 120 and 1600 times the maximum recommended human daily intranasal dose (MRHDID) on a mg/m^2 basis, respectively (see Data). In animal reproduction studies with pregnant mice, rats, or rabbits, mometasone furoate caused increased fetal malformations and decreased fetal survival and growth following administration of doses that produced exposures approximately 1 to 16 times the MRHDID on a mcg/m^2 or AUC basis (see Data). However, experience with oral corticosteroids suggests that rodents are more prone to teratogenic effects from corticosteroid exposure than humans.

The estimated background risk of major birth defects and miscarriage for the indicated population is unknown. All pregnancies have a background risk of birth defect, loss, or other adverse outcomes. In the U.S. general population, the estimated background risk of major birth defects and miscarriages in clinically recognized pregnancies is 2% to 4% and 15% to 20%, respectively.

Data

Animal Data

No reproductive toxicology studies were conducted with RYALTRIS; however, studies are available for olopatadine hydrochloride and mometasone furoate, as described below.

Olopatadine hydrochloride

In an oral embryo-fetal development study, pregnant rats were dosed throughout the period of organogenesis at doses up to 600 mg/kg/day. Maternal toxicity, producing death and reduced maternal body weight gain was observed at 600 mg/kg/day (approximately 1200 times the MRHDID on a mg/m^2 basis). Olopatadine produced cleft palate at 60 mg/kg/day (approximately 120 times the MRHDID on a mg/m^2 basis) and decreased embryo-fetal viability and reduced fetal weight in rats at 600 mg/kg/day (approximately 1200 times the MRHDID on a mg/m^2 basis).

In an oral embryo-fetal development study, pregnant rabbits were dosed throughout the period of organogenesis at doses up to 400 mg/kg/day. A decrease in the number of live fetuses was observed at 400 mg/kg/day (approximately 1600 times the MRHDID on a mg/m^2 basis).

In peri-/post-natal toxicity studies, pregnant rats received oral doses of olopatadine up to 600 mg/kg/day during late gestation and throughout the lactation period. Olopatadine produced decreased neonatal survival at 60 mg/kg/day (approximately 120 times the MRHDID on a mg/m^2 basis) and reduced body weight gain in pups at 4 mg/kg/day (approximately 7 times the MRHDID on a mg/m^2 basis). These effects appeared attributable to exposure of pups via the milk as demonstrated in a cross-fostered study in which pups of untreated dams cross-fostered to dams treated with 60 mg/kg/day olopatadine orally during the lactation period exhibited decreased body weight gain.

Mometasone furoate

In an embryo-fetal development study with pregnant mice dosed throughout the period of organogenesis, mometasone furoate produced cleft palate at a dose approximately equivalent to the MRHDID (on a mcg/m^2 basis with maternal subcutaneous doses of 60 mcg/kg and above) and decreased fetal survival at approximately 4 times the MRHDID (on a mcg/m^2 basis with a maternal subcutaneous dose of 180 mcg/kg). No toxicity was observed with a dose that produced an exposure approximately one-half of the MRHDID (on a mcg/m^2 basis with maternal topical dermal doses of 20 mcg/kg and above).

In an embryo-fetal development study with pregnant rats dosed throughout the period of organogenesis, mometasone furoate produced fetal umbilical hernia at exposures approximately 20 times the MRHDID (on a mcg/m^2 basis with maternal topical dermal doses of 600 mcg/kg and above) and delays in fetal ossification at a dose approximately 12 times the MRHDID (on a mcg/m^2 basis with maternal topical dermal doses of 300 mcg/kg and above).

In another reproductive toxicity study, pregnant rats were dosed with mometasone furoate throughout pregnancy or late in gestation. Treated animals had prolonged and difficult labor, fewer live births, lower birth weight, and reduced early pup survival at a dose that was approximately equivalent to the MRHDID (on a mcg/m^2 basis with a maternal subcutaneous dose of 15 mcg/kg). There were no findings at a dose approximately equivalent to or less than the MRHDID (on a mcg/m^2 basis with a maternal subcutaneous dose of 7.5 mcg/kg).

Embryo-fetal development studies were conducted with pregnant rabbits dosed with mometasone furoate by either the topical dermal route or oral route throughout the period of organogenesis. In the study using the topical dermal route, mometasone furoate caused multiple malformations in fetuses (e.g., flexed front paws, gallbladder agenesis, umbilical hernia, hydrocephaly) at doses approximately 12 times the MRHDID (on a mcg/m^2 basis with maternal topical dermal doses of 150 mcg/kg and above). In the study using the oral route, mometasone furoate caused increased fetal resorptions and cleft palate and/or head malformations (hydrocephaly and domed head) at a dose approximately 60 times the MRHDID (on a mcg/m^2 basis with a maternal oral dose of 700 mcg/kg). At approximately 220 times the MRHDID (on a mcg/m^2 basis with a maternal oral dose of 2800 mcg/kg), most litters were aborted or resorbed. No effects were observed at a dose approximately 12 times the MRHDID (on a mcg/m^2 basis with a maternal oral dose of 140 mcg/kg).

8.2 Lactation

Risk Summary

There are no available data on the presence of olopatadine or mometasone furoate or its metabolites in human milk, the effects on the breastfed child, or the effects on milk production. Other corticosteroids similar to mometasone furoate, are excreted in human milk. However, mometasone furoate concentrations in plasma after nasal therapeutic doses are low and therefore concentrations in human breast milk are likely to be correspondingly low.

Olopatadine has been identified in the milk of nursing rats following oral administration. It is not known whether topical nasal administration could result in sufficient systemic absorption to produce detectable quantities in human breast milk.

The developmental and health benefits of breastfeeding should be considered along with the mother’s clinical need for RYALTRIS and any potential adverse effects on the breast fed infant from RYALTRIS or from the underlying maternal condition.

8.4 Pediatric Use

The safety and effectiveness of RYALTRIS for the treatment of symptoms associated with seasonal allergic rhinitis have been established in pediatric patients 12 years and older. Use of RYALTRIS for this indication is supported by evidence from adequate and well-controlled studies in adult and pediatric patients 12 years and older [see Clinical Studies (14)].

The safety and effectiveness of RYALTRIS in pediatric patients below the age of 12 years have not been established.

Effect on Growth

Controlled clinical studies have shown that nasal corticosteroids may cause a reduction in growth velocity in pediatric patients. This effect has been observed in the absence of laboratory evidence of HPA axis suppression, suggesting that growth velocity is a more sensitive indicator of systemic corticosteroid exposure in pediatric patients than some commonly used tests of HPA axis function. The long-term effects of this reduction in growth velocity associated with nasal corticosteroids, including the impact on final adult height, are unknown. The potential for “catch up” growth following discontinuation of treatment with nasal corticosteroids has not been adequately studied.

The growth of pediatric patients receiving nasal corticosteroids, including RYALTRIS, should be monitored routinely (e.g., via stadiometry). The potential growth effects of prolonged treatment should be weighed against clinical benefits obtained and the risk/benefits of non-corticosteroid treatment alternatives.

The potential of mometasone furoate nasal spray 50 mcg to cause growth suppression in susceptible patients or when given at higher doses cannot be ruled out.

8.5 Geriatric Use

There were 20 patients 65 years of age and older treated with RYALTRIS in the clinical studies for seasonal allergic rhinitis [see Clinical Studies (14)]. Of the RYALTRIS-treated patients in these studies, 16 (2.7%) were between 65 to 75 years of age, while 4 (0.7%) were 75 years of age and older.

Clinical studies of RYALTRIS did not include sufficient numbers of patients 65 years of age and older to determine whether they respond differently from younger adult patients.

8.6 Hepatic Impairment

No studies have been conducted with RYALTRIS in patients with hepatic impairment. However, there have been reports of concentrations of mometasone furoate appearing to increase with severity of hepatic impairment [see Clinical Pharmacology (12.3)].

10 OVERDOSAGE

RYALTRIS contains both olopatadine hydrochloride and mometasone furoate; therefore, the risks associated with overdosage for the individual components described below apply to RYALTRIS.

Olopatadine Hydrochloride: Symptoms of antihistamine overdose may include drowsiness in adults and children. Agitation and restlessness, followed by drowsiness in children. Should overdose occur, symptomatic or supportive treatment is recommended.

Mometasone Furoate: Chronic overdosage with any corticosteroid may result in signs or symptoms of hypercorticism [see Warnings and Precautions (5.6)].

11 DESCRIPTION

RYALTRIS is a metered-dose manual nasal spray unit containing an aqueous suspension of a fixed‑dose combination of a histamine-1 (H1) receptor inhibitor (olopatadine hydrochloride) and a corticosteroid (mometasone furoate monohydrate).

Olopatadine hydrochloride is a white, sparingly water‑soluble crystalline powder. The chemical name for olopatadine hydrochloride is 2‑[(11Z)-11-[3-(dimethylamino)propylidene]-6H-benzo[c][1]benzoxepin-2-yl]acetic acid hydrochloride. It has a molecular weight of 373.88, and its molecular formula is C21H23NO3•HCl with the following chemical structure:

Mometasone furoate monohydrate is an anti-inflammatory corticosteroid having the chemical name [(8S,9R,10S,11S,13S,14S,16R,17R)-9-chloro-17-(2-chloroacetyl)-11-hydroxy-10,13,16-trimethyl-3-oxo-6,7,8,11,12,14,15,16-octahydrocyclopenta[a]phenanthren-17-yl] furan-2-carboxylate;hydrate and the following chemical structure:

Mometasone furoate monohydrate is a white powder, with an empirical formula of C27H30Cl2O6•H2O and a molecular weight of 539.45. It is practically insoluble in water; slightly soluble in methanol, ethanol, and isopropanol; soluble in acetone and chloroform; and freely soluble in tetrahydrofuran. Its partition coefficient between octanol and water is >5000.

RYALTRIS is a nasal spray containing an isotonic aqueous suspension of olopatadine hydrochloride (equivalent to 0.6% w/v olopatadine base) and mometasone furoate monohydrate (equivalent to 0.025% w/w mometasone furoate on the anhydrous basis). After initial priming (6 sprays), each metered spray delivers 100 microliters of suspension containing 665 mcg of olopatadine hydrochloride (equivalent to 600 mcg olopatadine base) and 25 mcg of mometasone furoate. RYALTRIS also contains benzalkonium chloride, carboxymethyl cellulose sodium, dibasic sodium phosphate heptahydrate, edetate disodium, hydrochloric acid, microcrystalline cellulose, polysorbate 80, sodium chloride, sodium hydroxide, and water. It has a pH of approximately 3.7 [see How Supplied/Storage and Handling (16)].

12 CLINICAL PHARMACOLOGY

12.1 Mechanism of Action

RYALTRIS contains both olopatadine hydrochloride and mometasone furoate. The mechanisms of action described below for the individual components apply to RYALTRIS.

Olopatadine Hydrochloride

Olopatadine is a histamine-1 (H1) receptor inhibitor. The antihistaminic activity of olopatadine has been documented in isolated tissues, animal models, and humans.

Mometasone Furoate

Mometasone furoate is a corticosteroid demonstrating potent anti-inflammatory activity. The precise mechanism of corticosteroid action on allergic rhinitis is not known. Corticosteroids have been shown to have a wide range of inhibitory effects on multiple cell types (e.g., mast cells, eosinophils, neutrophils, macrophages, and lymphocytes) and mediators (e.g., histamine, eicosanoids, leukotrienes, and cytokines) involved in inflammation.

12.2 Pharmacodynamics

Cardiac Electrophysiology

A study specifically designed to evaluate the effect of RYALTRIS on the QT interval has not been conducted.

In a 12-month study, 429 patients treated with olopatadine hydrochloride two sprays per nostril (665 mcg per spray) twice daily, no evidence of any effect of olopatadine hydrochloride on QT prolongation has been observed.

HPA Axis Effect

A study specifically designed to evaluate the effect of RYALTRIS on the HPA axis has not been conducted.

In one study, daily nasal doses of 200 and 400 mcg of mometasone furoate and oral dose of 10 mg prednisone were compared to placebo in 64 patients (22 to 44 years of age) with allergic rhinitis. Adrenal function before and after 36 consecutive days of treatment was assessed by measuring plasma cortisol levels following a 6-hour cosyntropin infusion and by measuring 24-hour urinary free cortisol levels. Mometasone furoate at both the 200- and 400-mcg dose, was not associated with a statistically significant decrease in mean plasma cortisol levels post-cosyntropin infusion or a statistically significant decrease in the 24-hour urinary free cortisol levels compared to placebo. A statistically significant decrease in the mean plasma cortisol levels post-cosyntropin infusion and 24-hour urinary free cortisol levels was detected in the prednisone treatment group compared to placebo.

12.3 Pharmacokinetics

Absorption

After repeated nasal administration of 2 sprays per nostril of RYALTRIS (2660 mcg of olopatadine hydrochloride and 100 mcg of mometasone furoate) twice daily in patients with seasonal allergic rhinitis, the mean (± standard deviation) peak plasma exposure (Cmax) was 19.80 ± 7.01 ng/mL for olopatadine and 9.92 ± 3.74 pg/mL for mometasone furoate, and the mean exposure over the dosing regimen (AUCtau) was 88.77 ± 23.87 ng/mL*hr for olopatadine and 58.40 ± 27.00 pg/mL*hr for mometasone furoate. The median time to peak exposure from a single dose was 1 hour for both olopatadine and mometasone furoate.

Distribution

The protein binding of olopatadine was moderate at approximately 55% in human serum and independent of drug concentration over the range of 0.1 to 1000 ng/mL. Olopatadine binds predominately to human serum albumin.

The in vitro protein binding for mometasone furoate was reported to be 98% to 99% in concentration range of 5 to 500 ng/mL.

Elimination

Following single‑dose nasal administration of a combination of olopatadine and mometasone furoate, the mean elimination half-lives of olopatadine and mometasone furoate were 9 and 18 hours, respectively.

Olopatadine is mainly eliminated through urinary excretion. Approximately 70% of a [^14C] olopatadine hydrochloride oral dose was recovered in urine with 17% in the feces. Of the drug‑related material recovered within the first 24 hours in the urine, 86% was unchanged olopatadine, with the balance comprised of olopatadine N-oxide and N-desmethyl olopatadine.

Any absorbed drug is excreted as metabolites mostly via the bile, and to a limited extent, into the urine.

Metabolism

Olopatadine is not extensively metabolized. Based on plasma metabolite profiles following oral administration of [^14C] olopatadine, at least 6 minor metabolites circulate in human plasma. Olopatadine accounts for 77% of peak plasma total radioactivity and all metabolites amounted to <6% combined. Two of these have been identified as the olopatadine N-oxide and N-desmethyl olopatadine. In in vitro studies with cDNA-expressed human CYP isoenzymes and flavin-containing monooxygenases (FMO), N-desmethyl olopatadine (Ml) formation was catalyzed mainly by CYP3A4, while olopatadine N-oxide (M3) was primarily catalyzed by FMO1 and FMO3. Olopatadine at concentrations up to 33900 ng/mL did not inhibit the in vitro metabolism of specific substrates for CYP1A2, CYP2C9, CYP2C19, CYP2D6, CYP2E1, and CYP3A4. The potential for olopatadine and its metabolites to act as inducers of CYP enzymes has not been evaluated.

Studies have shown that any portion of a mometasone furoate dose that is swallowed and absorbed undergoes extensive metabolism to multiple metabolites. There are no major metabolites detectable in plasma. Upon in vitro incubation, one of the minor metabolites formed is 6ß-hydroxy-mometasone furoate. In human liver microsomes, the formation of the metabolite is regulated by CYP3A4.

Specific Populations

No pharmacokinetic studies were performed in specific populations with RYALTRIS. The pharmacokinetics of the combination of olopatadine and mometasone furoate is expected to reflect that of the individual components, as the pharmacokinetics of the combination was found to be comparable to the individual components.

Patients with Hepatic Impairment: No specific pharmacokinetic study examining the effect of hepatic impairment was conducted. Metabolism of olopatadine is a minor route of elimination.

Administration of a single inhaled dose of 400 mcg mometasone furoate to subjects with mild (n=4), moderate (n=4), and severe (n=4) hepatic impairment resulted in only 1 or 2 subjects in each group having detectable peak plasma concentrations of mometasone furoate (ranging from 50 to 105 pcg/mL). The observed peak plasma concentrations appeared to increase with severity of hepatic impairment; however, the numbers of detectable levels were few.

Patients with Renal Impairment: The mean Cmax values for olopatadine following single nasal doses were not markedly different between healthy subjects (18.1 ng/mL) and patients with mild, moderate, and severe renal impairment (ranging from 15.5 to 21.6 ng/mL). Mean plasma AUC0-12 was 2‑fold higher in patients with severe impairment (creatinine clearance <30 mL/min/1.73 m^2). In these patients, peak steady-state plasma concentrations of olopatadine were approximately 10‑fold lower than those observed after higher, 20mg oral doses, twice daily, which were well tolerated.

The effects of renal impairment on mometasone furoate pharmacokinetics have not been adequately investigated.

Pediatric Patients: RYALTRIS pharmacokinetics has not been investigated in patients under 12 years of age [see Use in Specific Populations (8.4)]. Based on population pharmacokinetic analysis among patients 12 years of age and older, the pharmacokinetics of olopatadine and mometasone furoate with RYALTRIS was not influenced by age.

Male and Female Patients: Based on population pharmacokinetic analysis, the pharmacokinetics of olopatadine and mometasone furoate with RYALTRIS was not influenced by gender.

Racial or Ethnic Groups: Based on population pharmacokinetic analysis, the pharmacokinetics of olopatadine and mometasone furoate with RYALTRIS was not influenced by race.

Drug Interaction Studies

There were no clinically relevant differences in the pharmacokinetics of either olopatadine or mometasone furoate when administered in combination compared with administration alone.

Olopatadine: Drug interactions with inhibitors of liver enzymes are not anticipated because olopatadine is eliminated predominantly by renal excretion. Olopatadine did not inhibit the in vitro metabolism of specific substrates for CYP1A2, CYP2C9, CYP2C19, CYP2D6, CYP2E1, and CYP3A4. Based on these data, drug interactions involving P450 inhibition are not expected. Due to the modest protein binding of olopatadine (55%), drug interactions through displacement from plasma proteins are also not expected.

Mometasone Furoate: Inhibitors of CYP3A4: In a drug interaction study, an inhaled dose of mometasone furoate 400 mcg was given to 24 healthy subjects twice daily for 9 days, and ketoconazole 200 mg (as well as placebo) were given twice daily concomitantly on Days 4 to 9. Mometasone furoate plasma concentrations were <150 pcg/mL on Day 3 prior to coadministration of ketoconazole or placebo. Following concomitant administration of ketoconazole, 4 out of 12 subjects in the ketoconazole treatment group (n=12) had peak plasma concentrations of mometasone furoate >200 pcg/mL on Day 9 (211-324 pcg/mL).

13 NONCLINICAL TOXICOLOGY

13.1 Carcinogenesis, Mutagenesis, Impairment of Fertility

No studies of carcinogenicity, mutagenicity, or impairment of fertility were conducted with RYALTRIS; however, studies are available for the individual active components, olopatadine hydrochloride and mometasone furoate, as described below.

Olopatadine Hydrochloride: Olopatadine demonstrated no tumorigenic potential in mice at oral doses up to 500 mg/kg/day (approximately 510 times the MRHDID on a mg/m^2 basis) for 78 weeks or in rats at oral doses up to 200 mg/kg/day (approximately 410 times the MRHDID on a mg/m^2 basis) for 104 weeks.

No mutagenic potential was observed when olopatadine was tested in an in vitro bacterial reverse mutation (Ames) test, an in vitro mammalian chromosome aberration assay, or an in vivo mouse micronucleus test.

Olopatadine administered at an oral dose of 400 mg/kg/day, (approximately 810 times the MRHDID for adults on a mg/m^2 basis) produced toxicity in male and female rats, and resulted in a decrease in the fertility index and reduced implantation rate. No effects on reproductive function were observed at 50 mg/kg/day (approximately 100 times the MRHDID on a mg/m^2 basis).

Mometasone Furoate: In a 2-year carcinogenicity study in Sprague Dawley rats, mometasone furoate demonstrated no statistically significant increase in the incidence of tumors at inhalation doses up to 67 mcg/kg (approximately 2 times the MRHDID on a mcg/m^2 basis). In a 19‑month carcinogenicity study in Swiss CD-1 mice, mometasone furoate demonstrated no statistically significant increase in the incidence of tumors at inhalation doses up to 160 mcg/kg (approximately 4 times the MRHDID on a mcg/m^2 basis).

Mometasone furoate increased chromosomal aberrations in an in vitro Chinese hamster ovary‑cell assay, but did not increase chromosomal aberrations in an in vitro Chinese hamster lung cell assay. Mometasone furoate was not mutagenic in the Ames test or mouse lymphoma assay, and was not clastogenic in an in vivo mouse micronucleus assay and a rat bone marrow chromosomal aberration assay, or a mouse male germ-cell chromosomal aberration assay. Mometasone furoate also did not induce unscheduled DNA synthesis in vivo in rat hepatocytes.

In reproductive studies in rats, impairment of fertility was not produced by subcutaneous doses up to 15 mcg/kg (approximately equivalent to the MRHDID on a mcg/m^2 basis).

14 CLINICAL STUDIES

The efficacy of RYALTRIS was evaluated in two multicenter, randomized, double-blind, placebo-and active-controlled clinical studies of 2-week duration in Study 1 (NCT02631551) and Study 2 (NCT02870205). The two studies were of similar design, including a single blind, placebo run-in period for 7 to 10 days, and enrolled a total of 2352 patients 12 years of age and older with seasonal allergic rhinitis. Patients had a history of seasonal allergic rhinitis for at least 2 years prior to screening, a positive skin prick test (wheal diameter 5mm or greater than negative diluent control) to relevant seasonal allergens (tree/grass pollen in Study 1 and ragweed/mountain cedar pollen in Study 2), and nasal symptoms defined as a 12-hour rTNSS ≥8 out of 12 and a congestion score ≥2 for the morning (AM) assessment at screening.

In Studies 1 and 2, patients were randomized to 1 of 4 treatment groups: RYALTRIS 2 sprays (665 mcg olopatadine hydrochloride and 25 mcg mometasone furoate per spray) per nostril twice daily, olopatadine hydrochloride nasal spray 2 sprays (665 mcg per spray) per nostril twice daily, mometasone furoate nasal spray 2 sprays (25 mcg per spray) per nostril twice daily, and vehicle placebo for 2 weeks. The olopatadine hydrochloride and mometasone furoate comparators used the same device and vehicle as RYALTRIS but were non-US approved drugs. The demographics in Studies 1 and 2 were similar as shown in Table 2.

Table 2: Study 1 and Study 2 - Summary of Demographics
 | Study 1 (N=1180) | Study 2 (N=1172)
Age
Mean (SD) | 39 (15) | 40 (15)
Min, Max | 12, 87 | 12, 82
Age Group n (%)
12-17 | 115 (10) | 94 (8)
Race n (%)
White | 915 (78) | 956 (82)
Asian | 20 (2) | 22 (2)
American Indian or Alaska Native | 3 (0.3) | 3 (0.3)
Black or African American | 230 (20) | 181 (15)
Native Hawaiian or Other Pacific Islander | 4 (0.3) | 1 (<0.1)
Other* | 8 (0.7) | 9 (0.8)
Ethnicity n (%)
Hispanic or Latino | 279 (24) | 329 (28)
Gender n (%)
Female | 762 (65) | 737 (63)

N = number of subjects in study; n=number of subjects with data available; Min=minimum; Max=maximum; SD=standard deviation. % is based on N (total number of patients in the study)

*Other = Study 1: undefined and Study 2: White and American Indian, Multi-Racial, Mixed, African American and Caucasian, Caucasian and Hispanic, Pakistan and Caucasian.

The primary endpoint for both studies was the change from baseline in average morning (AM) and evening (PM) subject reported 12-hour reflective total nasal symptom score (rTNSS) over the 14-day treatment period. Secondary endpoints included change from baseline in average AM and PM subject-reported 12-hour instantaneous total nasal symptom score (iTNSS) over the 14‑day treatment period and change from baseline in average AM and PM subject-reported 12‑hour reflective total ocular symptom score (rTOSS) over the 14-day treatment period. The rTNSS and iTNSS were calculated as the sum of the patient-reported symptom scores of 4 individual nasal symptoms (rhinorrhea, nasal congestion, sneezing, and nasal itching) on a 0 to 3 categorical severity scale (0=absent, 1=mild, 2=moderate, and 3=severe). Similarly, rTOSS and iTOSS were calculated as the sum of patient’s scoring of 3 individual ocular symptoms (itching/burning, tearing/watering, and redness) on a 0 to 3 categorical severity scale (0=absent, 1=mild, 2=moderate, and 3=severe). Patients were required to record symptom severity daily (morning [AM] and evening [PM]), reflecting over the previous 12 hours (reflective) or at the time of dosing (instantaneous). The primary efficacy endpoint was the mean change from baseline in average AM and PM patient-reported 12-hour rTNSS over the 2-week treatment period. The average AM and PM rTNSS (maximum score of 12) was assessed as the change from baseline for each day and then averaged over a 2-week treatment period.

In both studies, treatment with RYALTRIS resulted in a statistically significant improvement in rTNSS compared to olopatadine hydrochloride and to mometasone furoate as well as to placebo (except for Study 1 comparison to mometasone furoate, 95% CI -0.8-0.0). Results from both studies are shown in Table 3.

Table 3: Mean Change from Baseline in Reflective Total Nasal Symptom Scores Over 2 Weeks* in Adults and Pediatric Patients ≥ 12 Years with Seasonal Allergic Rhinitis in Study 1 and Study 2
Treatment (2 sprays / nostril twice daily) | Study 1 |  |  |  | Study 2
Treatment (2 sprays / nostril twice daily) | N | Baseline Mean | Change From Baseline LS Mean | Treatment Effect Difference LS Mean, (95% CI) | N | Baseline Mean | Change From Baseline LS Mean | Treatment Effect Difference LS Mean, (95% CI)
RYALTRIS | 299 | 10.1 | -3.5 | -- | 291 | 10.1 | ‑3.5 | --
Olopatadine HCl nasal spray‡ | 294 | 10.3 | -2.9 | -0.6 † (-1.0, -0.2) | 290 | 10.2 | ‑3.1 | ‑0.4, †; (‑0.8, ‑0.1)
Mometasone furoate nasal spray‡ | 294 | 10.2 | -3.1 | -0.4 (-0.8, 0.0) | 293 | 10.2 | ‑3.1 | ‑0.5, †; (‑0.9, ‑0.1)
Placebo | 283 | 10.2 | -2.5 | -1.0, † (-1.3, -0.6) | 290 | 10.3 | ‑2.4 | ‑1.1, †; (‑1.5, ‑0.7)

* Average of AM and PM rTNSS for each day (maximum score = 12) and averaged over the 2-week treatment period.

† Statistically significant difference (p<0.05) using a gatekeeping strategy.

‡ Non-US approved drugs

Least Square (LS) Means, 95% Confidence Intervals (CIs), and p-values were based on the mixed model repeated measures model, adjusting for covariates that included treatment, site, baseline 12-hour reflective total nasal symptom score, and study day as the within-patient effect.

In the two studies, RYALTRIS also demonstrated statistically significant improvement in iTNSS as compared with placebo. Results from both studies are shown in Table 4.

Table 4: Mean Change from Baseline in Instantaneous Total Nasal Symptom Scores Over 2 Weeks* in Adults and Pediatric Patients ≥ 12 Years with Seasonal Allergic Rhinitis in Study 1 and Study 2
Treatment (2 sprays/nostril twice daily) | Study 1 |  |  |  | Study 2
Treatment (2 sprays/nostril twice daily) | N | Baseline Mean | Change From Baseline LS Mean | Treatment Effect Difference LS Mean, (95% CI) | N | Baseline Mean | Change From Baseline LS Mean | Treatment Effect Difference LS Mean, (95% CI)
RYALTRIS | 299 | 9.2 | -3.0 | -- | 291 | 9.2 | -3.1 | --
Olopatadine HCl nasal spray‡ | 294 | 9.4 | -2.5 | -0.5 (-0.9, -0.2) | 290 | 9.4 | -2.7 | -0.4, † (-0.8, -0.0)
Mometasone furoate nasal spray‡ | 294 | 9.3 | -2.7 | -0.4 (-0.7, -0.0) | 293 | 9.4 | -2.6 | -0.5, † (-0.9, -0.1)
Placebo | 283 | 9.3 | -2.1 | -0.9, † (-1.3, -0.6) | 290 | 9.6 | -2.2 | -0.9, † (-1.3, -0.6)

* Average of AM and PM iTNSS for each day (maximum score = 12) and averaged over the 2-week treatment period.

† Statistically significant difference (p<0.05)

‡ Not commercially marketed

Least Square (LS) Means, 95% Confidence Intervals (CIs), and p-values were based on the mixed model repeated measures model, adjusting for covariates that included treatment, site, baseline 12-hour reflective total nasal symptom score, and study day as the within-patient effect.

RYALTRIS demonstrated statistically significant improvement compared with placebo in the change from baseline in average morning and evening patient-reported 12‑hour rTOSS (LS mean difference from placebo for Study 1: -0.5, 95% CI: -0.8, -0.2); for Study 2: ‑0.5, 95% CI: -0.8, -0.2) and iTOSS (LS mean difference for Study 1: -0.5, 95% CI: -0.8, -0.2); for Study 2: ‑0.5, 95% CI: -0.8, -0.2) over a 2‑week treatment period.

Onset of action, defined as the first time point after initiation of treatment when RYALTRIS demonstrated a statistically significant change from baseline in iTNSS compared with placebo, was assessed in both studies. Onset of action was observed within 15 minutes following the initial dose of RYALTRIS. Following the initial dose, iTNSS improved over the first week and was sustained through 2 weeks of treatment (Study 1).

The subjective impact of seasonal allergic rhinitis on a patient’s health-related quality of life was evaluated by the Rhinoconjunctivitis Quality of Life Questionnaire - Standardized Activities (RQLQ[S]) (28 questions in 7 domains [activities, sleep, non-nose/eye symptoms, practical problems, nasal symptoms, eye symptoms, and emotional] evaluated on a 7-point scale, in which 0=no impairment and 6=maximum impairment). An overall RQLQ(S) score is calculated from the mean of all items in the instrument. A change from baseline of at least 0.5 points is considered a clinically meaningful improvement. In each of these studies, treatment with RYALTRIS resulted in a statistically significant greater decrease from baseline in the overall RQLQ(S) than placebo (LS mean difference from placebo for Study 1: -0.5 [-0.8, -0.3]; for Study 2: ‑0.5 [95% CI: ‑0.7, ‑0.2]). In these studies, the treatment differences between RYALTRIS and the monotherapies were less than the minimum important difference of 0.5 points.

16 HOW SUPPLIED/STORAGE AND HANDLING

RYALTRIS (NDC 59467-700-27) is supplied in a white plastic bottle fitted with a metered‑dose spray nozzle unit. Each bottle contains a net fill weight of 31 g and will deliver 240 metered sprays in addition to six (6) initial priming sprays [see Description (11)].

Each spray delivers a volume of 0.1 mL suspension as a fine mist, containing 665 mcg of olopatadine hydrochloride equivalent to 600 mcg of olopatadine (base) and 25 mcg of mometasone furoate monohydrate (on the anhydrous basis). The bottle should be discarded after 240 sprays have been used.

Storage

Store RYALTRIS upright with the purple dust cap on at room temperature (see USP Controlled Room Temperature, between 20°C and 25°C, or between 68°F and 77°F, with excursions permitted between 15°C to 30°C or between 59°F to 86°F). Do not store in a freezer or refrigerator.

17 PATIENT COUNSELING INFORMATION

Advise the patient to read the FDA-approved patient labeling (Patient Information and Instructions for Use).

Local Nasal Adverse Reactions

Nasal antihistamines are associated with epistaxis, nasal ulceration, and nasal septal perforation. Nasal corticosteroids are associated with epistaxis, nasal septal perforation, Candida albicans infection, and impaired wound healing [see Warnings and Precautions (5.1)].

Somnolence and Impaired Mental Alertness

Patients should be cautioned against engaging in hazardous occupations requiring complete mental alertness and motor coordination such as driving or operating machinery after administration of RYALTRIS [see Warnings and Precautions (5.2)]. Somnolence has been reported in some patients (2 of 789 patients) taking RYALTRIS in controlled clinical studies in seasonal allergic rhinitis [see Adverse Reactions (6.1)].

Concurrent Use of Alcohol and Other Central Nervous System Depressants

Patients should be advised to avoid concurrent use of RYALTRIS with alcohol or other CNS depressants because additional reductions in alertness and additional impairment of CNS performance may occur [see Warnings and Precautions (5.2)].

Administration Information

Patients should be instructed to shake the bottle well before each use and prime RYALTRIS before initial use by releasing 6 sprays or until a fine mist appears. When RYALTRIS has not been used for 14 days or more, patients should re-prime with 2 sprays or until a fine mist appears. Patients should be instructed to avoid spraying RYALTRIS into their eyes [see Dosage and Administration (2)].

Glaucoma and Cataracts

Patients should be informed that nasal and inhaled corticosteroids may result in the development of glaucoma and/or cataracts. Therefore, close monitoring is warranted in patients with a change in vision or with a history of increased intraocular pressure, glaucoma, and/or cataracts [see Warnings and Precautions (5.3)].

Hypersensitivity Reactions

Hypersensitivity reactions can occur with RYALTRIS. Hypersensitivity reactions including wheezing, have occurred after the nasal administration of mometasone furoate. Discontinue RYALTRIS if such reactions occur [see Contraindications (4) and Warnings and Precautions (5.4)].

Immunosuppression and Risk of Infections

Persons who are on immunosuppressant doses of corticosteroids should be warned to avoid exposure to chickenpox or measles, and patients should also be advised that if they are exposed, medical advice should be sought without delay. Inform patients of potential worsening of existing tuberculosis; fungal, bacterial, viral, or parasitic infections; or ocular herpes simplex [see Warnings and Precautions (5.5)].

Potential Drug Interactions

Patients should be advised to be cautious if RYALTRIS is co-administered with ketoconazole or other known strong CYP3A4 inhibitors (e.g., ritonavir, cobicistat-containing products, atazanavir, clarithromycin, indinavir, itraconazole, nefazodone, nelfinavir, saquinavir, telithromycin) [see Drug Interactions (7.2)].

Distributed by:

Hikma Specialty USA Inc.

Columbus, OH 43228

RYALTRIS and the RYALTRIS logo are registered trademarks of Glenmark Specialty SA

Under license from Glenmark Specialty SA

Revised: April 2025

PN 141197

PATIENT INFORMATION

RYALTRIS (rye - al’ - tris)

(olopatadine hydrochloride and mometasone furoate monohydrate nasal spray)

Important: For use in your nose only. Do not spray RYALTRIS into your eyes or mouth.

What is RYALTRIS?

RYALTRIS is a prescription nasal spray that contains 2 medicines, olopatadine hydrochloride, an antihistamine, and mometasone furoate, a corticosteroid. RYALTRIS is used to treat symptoms of seasonal allergies in people 12 years of age and older.

It is not known if RYALTRIS is safe and effective in children under 12 years of age.

Do not use RYALTRIS if you are allergic to olopatadine hydrochloride, mometasone furoate monohydrate, or any of the ingredients in RYALTRIS. See the end of this Patient Information leaflet for a complete list of ingredients in RYALTRIS. Ask your healthcare provider if you are not sure.

Before you use RYALTRIS, tell your healthcare provider about all of your medical conditions, including if you:

- have had recent nasal sores, nasal surgery, or nasal injury.
- have eye or vision problems, such as cataracts or glaucoma (increased pressure in your eyes).
- have tuberculosis or any untreated fungal, bacterial, viral infections, or eye infections caused by herpes.
- have been near someone who has chickenpox or measles.
- are not feeling well or have any other symptoms that you do not understand.
- are pregnant or plan to become pregnant. It is not known if RYALTRIS will harm your unborn baby. Talk to your healthcare provider if you are pregnant or plan to become pregnant.
- are breastfeeding or plan to breastfeed. It is not known if RYALTRIS passes into your breast milk. Talk to your healthcare provider about the best way to feed your baby while using RYALTRIS.

Tell your healthcare provider about all the medicines you take, including prescription and over-the-counter medicines, vitamins, and herbal supplements.

Especially tell your healthcare provider if you take:

- certain medicines for HIV (such as ritonavir, atazanavir, indinavir, nelfinavir, and saquinavir)
- cobicistat-containing products
- certain antifungals (such as ketoconazole or itraconazole)
- certain antibiotics (such as clarithromycin and telithromycin)
- certain antidepressants (such as nefazodone)

RYALTRIS and other medicines may affect each other, causing side effects.

Know the medicines you take. Keep a list of your medicines and show it to your healthcare provider or pharmacist when you get a new medicine.

How should I use RYALTRIS?

- Read the Instructions for Use at the end of this Patient Information leaflet for information about the right way to use RYALTRIS.
- RYALTRIS is for use in your nose only. Do not spray it into your eyes or mouth.
- Use RYALTRIS exactly as your healthcare provider tells you to use it.
- If a child accidentally swallows RYALTRIS or you use too much RYALTRIS, call your healthcare provider or go to the nearest hospital emergency room right away.
- See your healthcare provider regularly to check your symptoms while using RYALTRIS and to check for side effects.

What should I avoid while using RYALTRIS?

- RYALTRIS can cause sleepiness or drowsiness. Do not drive, operate machinery, or do anything that needs you to be alert until you know how RYALTRIS affects you.
- Do not drink alcohol or take any other medicines that may cause you to feel sleepy while using RYALTRIS.

What are the possible side effects of RYALTRIS?

RYALTRIS may cause serious side effects, including the following:

- nose and throat problems. Symptoms of nose and throat problems may include:
  - nosebleeds
  - sores (ulcers) in the nose
  - hole in the cartilage between your nose (nasal septal perforation). Symptoms of nasal septal perforation may include:
    - crusting in the nose
    - nosebleeds
    - runny nose
    - whistling sound when you breathe
- slow wound healing. You should not use RYALTRIS until your nose has healed if you have a sore in your nose, if you have had surgery on your nose, or if your nose has been injured.
- thrush (Candida), a certain fungal infection in your nose and throat. Tell your healthcare provider if you have any redness or white-colored patches in your nose or mouth.
- eye problems, including glaucoma or cataracts. You should have regular eye exams when using RYALTRIS.
- allergic reactions. Call your healthcare provider or get emergency medical care if you get any of the following signs of a serious allergic reaction:

- wheezing
- rash
- hives

- swelling of your face, mouth, and tongue
- breathing problems

- immune system problems that may increase your risk of infections. Taking medicines that weaken your immune system makes you more likely to get infections. These infections may include tuberculosis (TB), ocular herpes simplex infections, and infections caused by fungi, bacteria, viruses, and parasites. Avoid contact with people who have contagious diseases, such as chickenpox or measles, while using RYALTRIS. If you come in contact with someone who has chicken pox or measles call your healthcare provider right away. Symptoms of infection may include:

- fever
- aches or pains

- chills
- feeling tired

- adrenal insufficiency. Adrenal insufficiency happens when your adrenal glands do not make enough steroid hormones. Symptoms of adrenal insufficiency can include:

- tiredness
- weakness
- nausea

- vomiting
- low blood pressure

- slowed growth in children. A child’s growth should be checked regularly while using RYALTRIS.
- sleepiness or drowsiness.

The most common side effects of RYALTRIS include the following:

- unpleasant taste
- nosebleeds
- nasal discomfort

Tell your healthcare provider if you have any side effects that bother you or that do not go away. These are not all of the possible side effects of RYALTRIS. For more information, ask your healthcare provider or pharmacist.

Call your doctor for medical advice about side effects. You may report side effects to FDA at 1‑800‑FDA‑1088.

How should I store RYALTRIS?

- Store RYALTRIS upright with the purple dust cap on at room temperature between 68°F to 77°F (20°C to 25°C).
- Do not freeze or refrigerate.
- Safely throw away medicine that is out of date or no longer needed.
- Throw away your RYALTRIS bottle after using 240 sprays after the first priming. Even though the bottle may not be completely empty, you may not get the correct dose of medicine if you continue to use it.

Keep RYALTRIS and all medicines out of reach of children.

General information about the safe and effective use of RYALTRIS

Medicines are sometimes prescribed for purposes other than those listed in the Patient Information. Do not use RYALTRIS for a condition for which it was not prescribed. Do not give RYALTRIS to other people, even if they have the same symptoms that you have. It may harm them.

You can ask your healthcare provider or pharmacist for information about RYALTRIS that is written for health professionals.

What are the ingredients in RYALTRIS?

Active ingredients: olopatadine hydrochloride and mometasone furoate monohydrate

Inactive ingredients: benzalkonium chloride, carboxymethyl cellulose sodium, dibasic sodium phosphate heptahydrate, edetate disodium, hydrochloric acid, microcrystalline cellulose, polysorbate 80, sodium chloride, sodium hydroxide, and water.

For more information, go to www.RYALTRIS.com or call Hikma Specialty USA Inc. at 1‑800‑962-8364.

This Patient Information has been approved by the U.S. Food and Drug Administration Issued: April 2025

INSTRUCTIONS FOR USE

RYALTRIS (rye - al’ - tris)
(olopatadine hydrochloride and mometasone furoate monohydrate nasal spray)

Important: For use in your nose only. Do not spray RYALTRIS into your eyes or mouth.

Read the Instructions for Use before you start to use RYALTRIS and each time you get a refill. There may be new information. This Instructions for Use does not take the place of talking with your healthcare provider about your medical condition or treatment. Before you use RYALTRIS, make sure your healthcare provider shows you the right way to use it.

Shake the bottle for at least 10 seconds before each use.

When RYALTRIS is not in use, the purple dust cap should always be kept tightly placed on the white nozzle tip.

Your RYALTRIS nasal spray bottle (See Figure A)

Figure A

Preparing the nasal spray bottle

Before you prime the bottle, shake the bottle for at least 10 seconds.

Before first use, spray the product 6 times or until a fine mist appears. Spray away from your eyes and face.

Step 1. Remove the purple dust cap from the spray nozzle tip of the bottle. (See Figure B)

Figure B

Preparing the nasal spray bottle

Step 2. Hold the nasal spray bottle firmly and upright with your index and middle finger on either side of the spray nozzle unit (on finger rests) while supporting the grooved base of the bottle with your thumb.

Step 3. Before first use, push down on the pump quickly and firmly 6 times, releasing the spray into the air, away from the eyes and face until a fine mist appears. (See Figure C)

Figure C

If you do not use RYALTRIS for 14 or more days, you will need to shake the bottle for at least 10 seconds, and prime the pump with 2 sprays or until a fine mist appears.

Your RYALTRIS is now ready for use.

Using your RYALTRIS

Step 4.

Gently blow your nose to clear your nostrils. (See Figure D)

Figure D

Step 5. Shake the bottle for at least 10 seconds before each use (morning and evening).

Step 6. Hold the bottle firmly with your index and middle finger on either side of the spray nozzle unit (on finger rests) while supporting the grooved base of the bottle with your thumb. (See Figure E)

Figure E

Step 7. Hold 1 nostril closed with a finger. Insert the end of the spray nozzle tip into the other nostril, pointing it slightly toward the outside of the nose, away from the nasal septum (the wall between the 2 nostrils). (See Figure F)

Figure F

Step 8. Tilt your head forward slightly. Keep the bottle upright and press down one time quickly and firmly on the finger rests to activate the pump. (See Figure G) Breathe in (inhale) gently through your nose as you spray. Then breathe out through your mouth.

Figure G

- Try not to get any spray into your eyes or directly on your nasal septum (the wall between the 2 nostrils).

Step 9. Repeat Steps 6 through 8 and deliver a second spray in the same nostril.

Step 10. Repeat Steps 6 through 8 with 2 sprays in the other nostril.

- Do not blow your nose for at least 15 minutes after using RYALTRIS, to make sure that you receive all of the medicine.
- Do not tip your head back. This will keep the medicine from going into your throat.

Step 11. To prevent any blockage, wipe the white spray nozzle tip with a clean dry tissue or cloth after each use. (See Figure H)

Figure H

Step 12. Hold the nozzle unit and push the purple dust cap back on the nozzle until you hear a click. (See Figure I)

Figure I

Each bottle of RYALTRIS contains enough medicine for you to spray from the bottle 240 times after the first (initial) priming. You should keep track of the number of sprays used from each bottle of RYALTRIS. Do not count any sprays used for initial priming of the bottle.

How to clear the RYALTRIS nozzle tip if it gets blocked

Do not try to unblock the spray nozzle tip by inserting a pin or other sharp object. (See Figure J) This will damage the spray nozzle tip, and you may not get the correct dose of medicine.

Figure J

Step 13. Remove the spray nozzle unit by gently pulling upward (See Figure K). Remove the purple dust cap and place only the spray nozzle unit in warm water to soak. (See Figure L)

Figure K

Figure L

Step 14. After soaking the spray nozzle tip for 15 minutes, rinse the spray nozzle unit and purple dust cap with warm water and allow them to dry completely. (See Figure M)

Figure M

Step 15. Place the purple dust cap back on the spray nozzle unit and put the spray nozzle unit back on the bottle. (See Figure N)

Figure N

Step 16. After following the steps to clear your blocked spray nozzle tip see “Priming your RYALTRIS pump before use” section above and re-prime using 2 sprays. Replace the purple dust cap, and your RYALTRIS is ready for use.

Repeat the unblocking steps if needed.

How should I store RYALTRIS?

Store RYALTRIS at room temperature between 68°F to 77°F (20°C to 25°C).

Do not freeze or refrigerate.

Do not use RYALTRIS after the expiration date on the label or the box.

Throw away your RYALTRIS bottle after using 240 sprays after first priming. Even though the bottle may not be completely empty, you may not get the correct dose of medicine if you continue to use it.

Keep RYALTRIS and all medicines out of the reach of children.

Distributed by:

Hikma Specialty USA Inc.
Columbus, OH 43228

RYALTRIS and the RYALTRIS logo are registered trademarks of Glenmark Specialty SA

Under license from Glenmark Specialty SA

This Instructions for Use has been approved by the U.S. Food and Drug Administration. April 2025